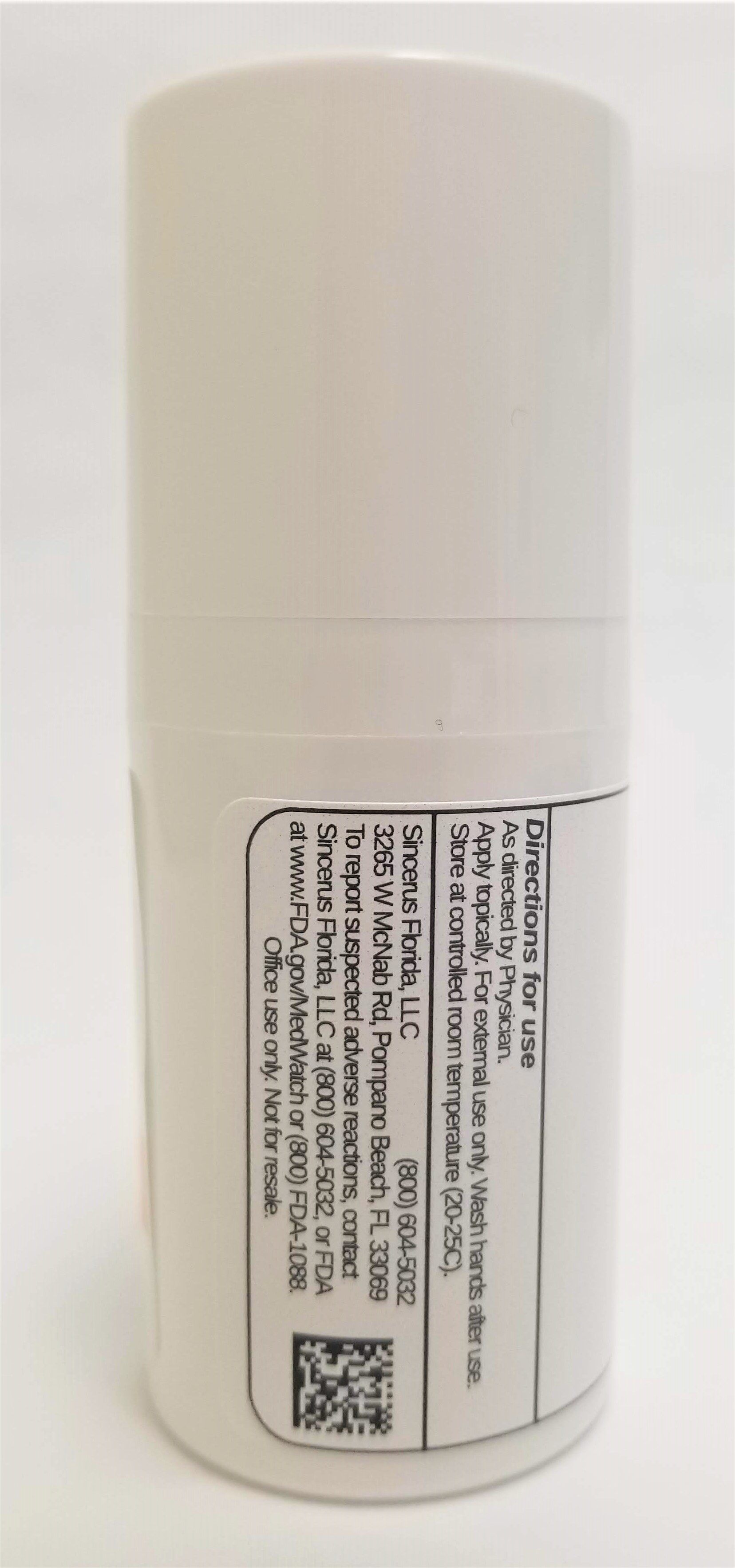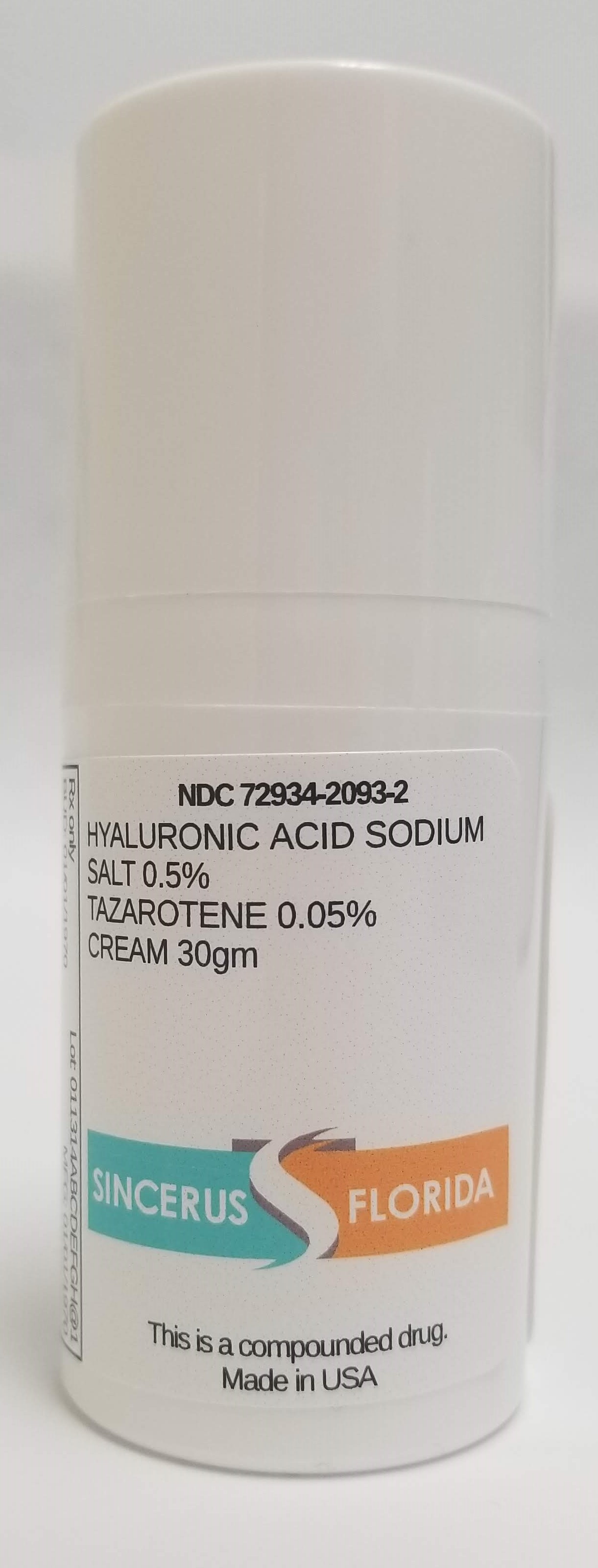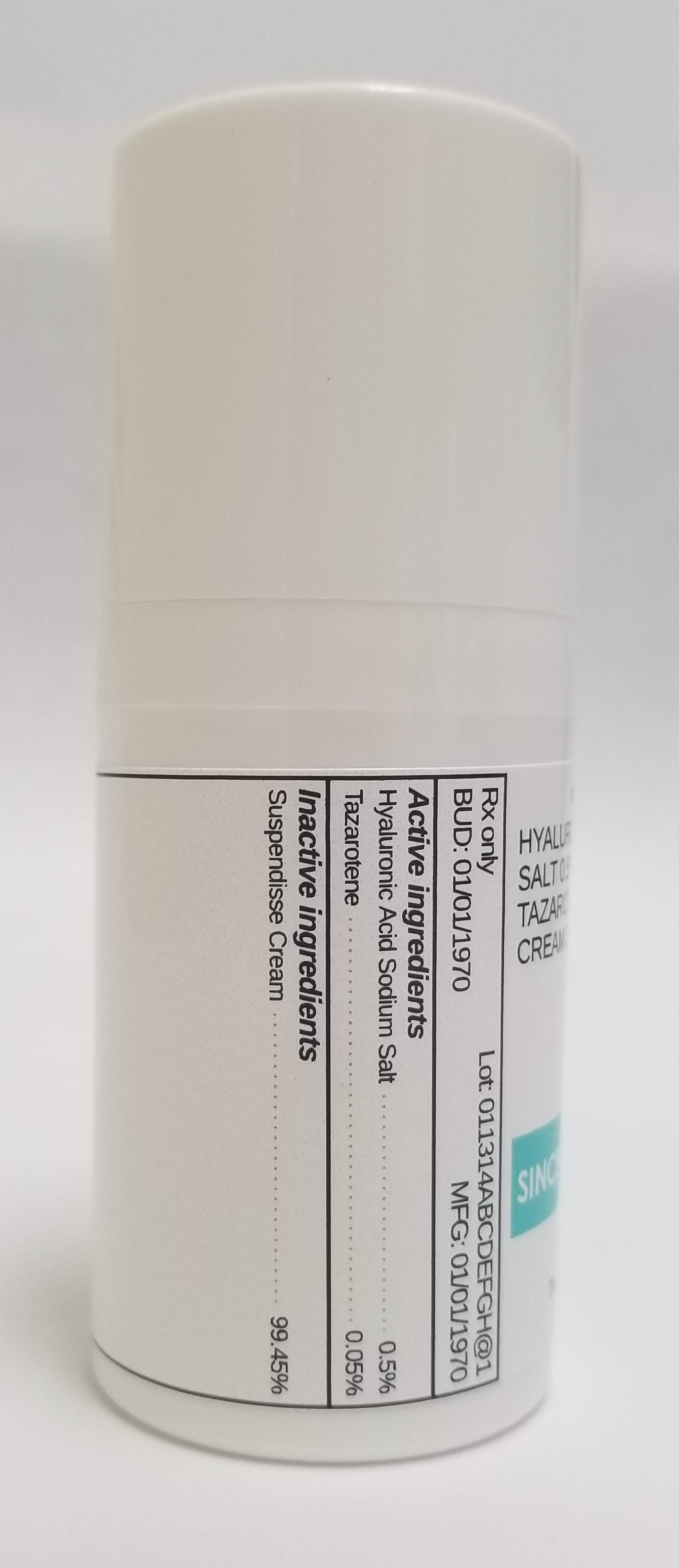 DRUG LABEL: HYALURONIC ACID SODIUM SALT 0.5% / TAZAROTENE 0.05%
NDC: 72934-2093 | Form: CREAM
Manufacturer: Sincerus Florida, LLC
Category: prescription | Type: HUMAN PRESCRIPTION DRUG LABEL
Date: 20190509

ACTIVE INGREDIENTS: TAZAROTENE 0.05 g/100 g; HYALURONATE SODIUM 0.5 g/100 g

HYALURONIC ACID SODIUM SALT 0.5% / TAZAROTENE 0.05%